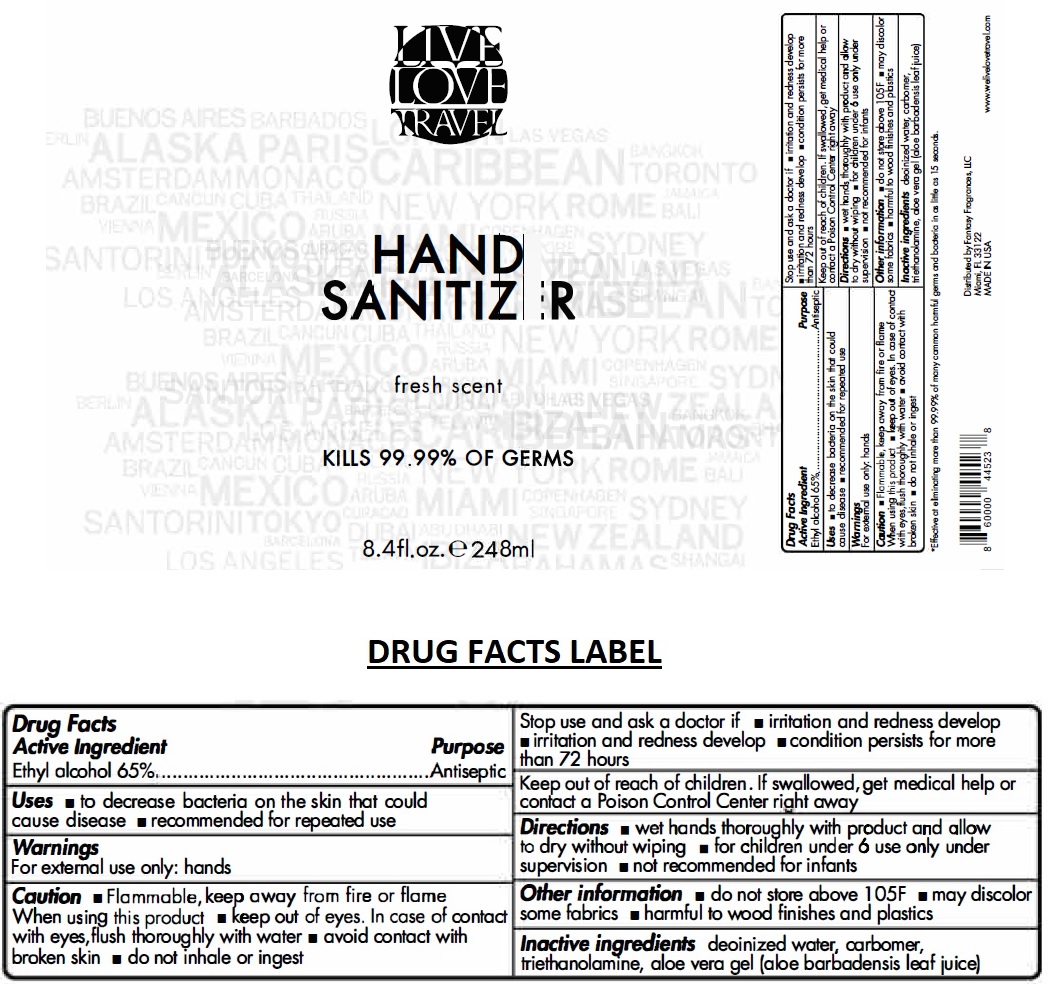 DRUG LABEL: Live Love Travel Hand Sanitizer
NDC: 80523-065 | Form: GEL
Manufacturer: Fantasy Fragrances Llc
Category: otc | Type: HUMAN OTC DRUG LABEL
Date: 20200930

ACTIVE INGREDIENTS: ALCOHOL 65 mL/100 mL
INACTIVE INGREDIENTS: WATER; CARBOMER HOMOPOLYMER, UNSPECIFIED TYPE; TROLAMINE; ALOE VERA LEAF

LIVE LOVE TRAVEL HAND SANITIZER

Active Ingredient

Ethyl alcohol 65%

Purpose

Antiseptic

INDICATIONS AND USAGE

Uses • to decrease bacteria on the skin that could cause disease • recommended for repeated use

Warnings

For external use only: hands

Caution • Flammable, keep away from fire or flame

When using this product • keep out of eyes. In case of contact with eyes, flush thoroughly with water • avoid contact with broken skin • do not inhale or ingest

Stop use and ask a doctor if • irritation and redness develop • condition persists for more than 72 hours

Keep out of reach of children. If swallowed, get medical help or contact a Poison Control Center right away

DOSAGE AND ADMINISTRATION

Directions • wet hands thoroughly with product and allow to dry without wiping • for children under 6 use only under supervision • not recommended for infants

Other information • do not store above 105F • may discolor some fabrics • harmful to wood finishes and plastics

INACTIVE INGREDIENT

Inactive ingredients deionized water, carbomer, triethanolamine, aloe vera gel (aloe barbadensis leaf juice)

fresh scent

KILLS 99.99% OF GERMS

*Effective at eliminating more than 99.99% of many common harmful germs and bacteria in as little as 15 seconds.

Distributed by Fantasy Fragrances, llC
Miami, FL 33122

MADE IN USA

www.welivelovetravel.com